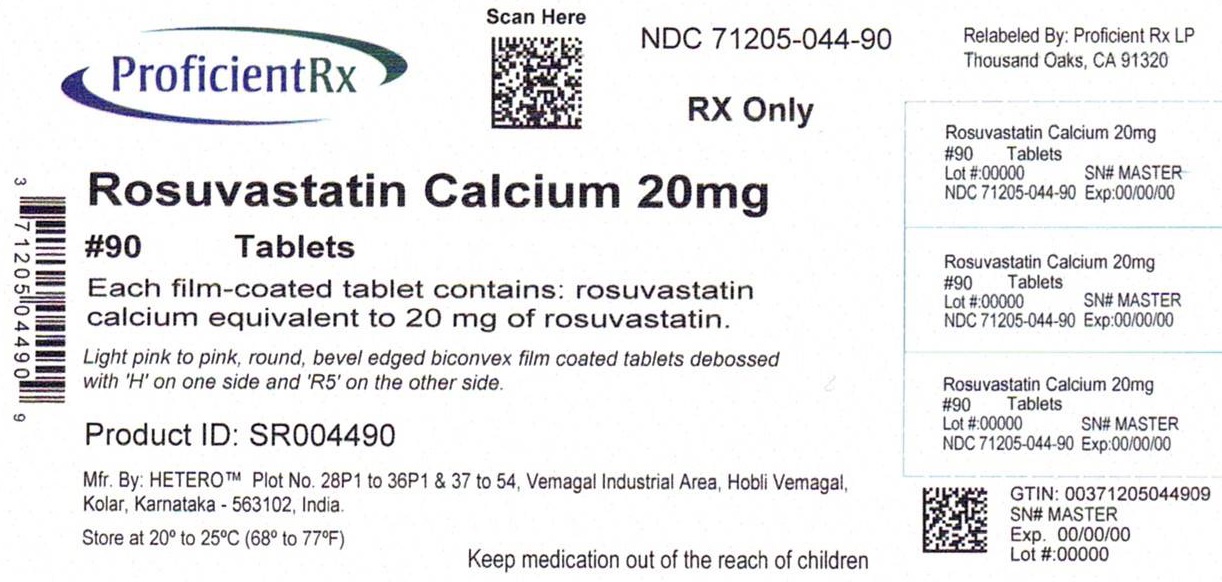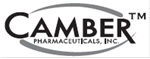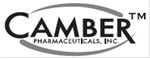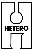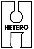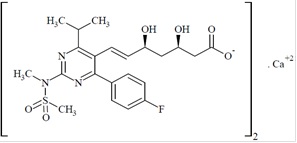 DRUG LABEL: Rosuvastatin
NDC: 71205-044 | Form: TABLET, FILM COATED
Manufacturer: Proficient Rx LP
Category: prescription | Type: HUMAN PRESCRIPTION DRUG LABEL
Date: 20250101

ACTIVE INGREDIENTS: ROSUVASTATIN CALCIUM 20 mg/1 1
INACTIVE INGREDIENTS: CROSPOVIDONE (120 .MU.M); FD&C BLUE NO. 2; FD&C RED NO. 40; HYDROXYPROPYL CELLULOSE (1600000 WAMW); HYPROMELLOSE, UNSPECIFIED; LACTOSE MONOHYDRATE; MAGNESIUM STEARATE; MICROCRYSTALLINE CELLULOSE; SODIUM BICARBONATE; TALC; TITANIUM DIOXIDE; TRIACETIN; FD&C YELLOW NO. 6

HIGHLIGHTS OF PRESCRIBING INFORMATION
These highlights do not include all the information needed to use ROSUVASTATIN CALCIUM TABLETS safely and effectively. See full prescribing information for ROSUVASTATIN CALCIUM TABLETS.
ROSUVASTATIN CALCIUM tablets, for oral use
Initial U.S. Approval: 2003

1 INDICATIONS & USAGE

Rosuvastatin calcium tablet is an HMG Co-A reductase inhibitor indicated for:

• adult patients with hypertriglyceridemia as an adjunct to diet (Error! Hyperlink reference not valid.)

• adult patients with primary dysbetalipoproteinemia (Type III hyperlipoproteinemia) as an adjunct to diet (Error! Hyperlink reference not valid.)

• adult patients with homozygous familial hypercholesterolemia (HoFH) to reduce LDL-C, total-C, and ApoB (Error! Hyperlink reference not valid.)

Limitations of use (Error! Hyperlink reference not valid.): Rosuvastatin calcium tablets have not been studied in Fredrickson Type I and V dyslipidemias.

2 DOSAGE & ADMINISTRATION

•Rosuvastatin calcium tablets can be taken with or without food, at any time of day. (Error! Hyperlink reference not valid.)

•Dose range: 5 to 40 mg once daily. Use 40 mg dose only for patients not reaching LDL-C goal with 20 mg. (Error! Hyperlink reference not valid.)

•Adult HoFH: Starting dose 20 mg/day (Error! Hyperlink reference not valid.)

3 DOSAGE FORMS & STRENGTHS

Tab let s: 5 m g, 10 m g, 20 m g, a nd 40 mg (Error! Hyperlink reference not valid.)

4 CONTRAINDICATIONS

•Known hypersensitivity to product components (Error! Hyperlink reference not valid.)

•Active liver disease, which may include unexplained persistent elevations in hepatic transaminase levels (Error! Hyperlink reference not valid.)

•Pregnancy (Error! Hyperlink reference not valid., Error! Hyperlink reference not valid., Error! Hyperlink reference not valid.)

•Lactation (Error! Hyperlink reference not valid., Error! Hyperlink reference not valid.)

5 WARNINGS AND PRECAUTIONS

Skeletal muscle effects (e.g., myopathy and rhabdomyolysis): Risks increase with use of 40 mg dose, advanced age (≥65), hypothyroidism, renal impairment, and combination use with cyclosporine, atazanavir/ritonavir, lopinavir/ritonavir, or simeprevir. Cases of myopathy and rhabdomyolysis with acute renal failure secondary to myoglobinuria have been reported. Advise patients to promptly report to their physician unexplained and/or persistent muscle pain, tenderness, or weakness and discontinue rosuvastatin calcium tablets if signs or symptoms appear. (Error! Hyperlink reference not valid., Error! Hyperlink reference not valid.,Error! Hyperlink reference not valid.)

• Liver enzyme abnormalities: Persistent elevations in hepatic transaminases can occur. Perform liver enzyme tests before initiating therapy and as clinically indicated thereafter. (Error! Hyperlink reference not valid.)

6 ADVERSE REACTIONS

Most frequent adverse reactions (rate ≥2%) are headache, myalgia, abdominal pain, asthenia, and nausea. (Error! Hyperlink reference not valid.)

To report SUSPECTED ADVERSE REACTIONS, contact Hetero Labs Limited at 1-866-495-1995 or FDA at 1-800-FDA-1088 or www.fda.gov/medwatch

7 DRUG INTERACTIONS

•Cyclosporine: Combination increases rosuvastatin exposure. Limit rosuvastatin calcium tablets dose to 5 mg once daily. (Error! Hyperlink reference not valid., Error! Hyperlink reference not valid., Error! Hyperlink reference not valid., Error! Hyperlink reference not valid.)

•Gemfibrozil: Combination should be avoided. If used together, limit rosuvastatin calcium tablets dose to 10 mg once daily. Error! Hyperlink reference not valid., Error! Hyperlink reference not valid., Error! Hyperlink reference not valid.)

•Atazanavir/ritonavir, lopinavir/ritonavir, or simeprevir: Combination increases rosuvastatin exposure. Limit rosuvastatin calcium tablets dose to 10 mg once daily. (Error! Hyperlink reference not valid., Error! Hyperlink reference not valid.,Error! Hyperlink reference not valid., Error! Hyperlink reference not valid.)

•Coumarin anticoagulants: Combination prolongs INR. Achieve stable INR prior to starting rosuvastatin calcium tablets. Monitor INR frequently until stable upon initiation or alteration of rosuvastatin calcium tablets therapy. (Error! Hyperlink reference not valid., Error! Hyperlink reference not valid.)

•Concomitant lipid-lowering therapies: Use with fibrates or lipid-modifying doses (≥1 g/day) of niacin increases the risk of adverse skeletal muscle effects. Caution should be used when prescribing with rosuvastatin calcium tablets. (Error! Hyperlink reference not valid., Error! Hyperlink reference not valid., Error! Hyperlink reference not valid.)

8 USE IN SPECIFIC POPULATIONS

•Females of reproductive potential: Advise females of reproductive potential to use effective contraception during treatment with rosuvastatin calcium tablets (Error! Hyperlink reference not valid.)

•Severe renal impairment (not on hemodialysis): Starting dose is 5 mg, not to exceed 10 mg. (Error! Hyperlink reference not valid.,Error! Hyperlink reference not valid., Error! Hyperlink reference not valid.)

•Asian population: Consider 5 mg starting dose. (Error! Hyperlink reference not valid., Error! Hyperlink reference not valid.)

See 17 for PATIENT COUNSELING INFORMATION and FDA- approved patient labeling.

Pediatric use information for patients ages 7 to 17 years of age is approved for AstraZeneca’s CRESTOR (rosuvastatin calcium) tablets. However, due to AstraZeneca’s marketing exclusivity rights, this drug product is not labeled with that pediatric information.

FULL PRESCRIBING INFORMATION

1 INDICATIONS & USAGE

Pediatric use information for patients 7 to 17 years of age is approved for AstraZeneca’s CRESTOR (rosuvastatin calcium) tablets. However, due to AstraZeneca’s marketing exclusivity rights, this drug product is not labeled with that pediatric information.

1.3 Hypertriglyceridemia

Rosuvastatin calcium tablets are indicated as adjunctive therapy to diet for the treatment of adult patients with hypertriglyceridemia.

1.4 Primary Dysbetalipoproteinemia (Type III Hyperlipoproteinemia)

Rosuvastatin calcium tablets are indicated as an adjunct to diet for the treatment of adult patients with primary dysbetalipoproteinemia (Type III Hyperlipoproteinemia).

1.5 Adult Patients with Homozygous Familial Hypercholesterolemia

Rosuvastatin calcium tablets are indicated as adjunctive therapy to other lipid-lowering treatments (e.g., LDL apheresis) or alone if such treatments are unavailable to reduce LDL-C, Total-C, and ApoB in adult patients with homozygous familial hypercholesterolemia.

1.8 Limitations of Use

Rosuvastatin calcium tablets have not been studied in Fredrickson Type I and V dyslipidemias.

2 DOSAGE & ADMINISTRATION

2.1 General Dosing Information

The dose range for rosuvastatin calcium tablets in adults are 5 to 40 mg orally once daily. The usual starting dose is 10 to 20 mg once daily. The usual starting dose in adult patients with homozygous familial hypercholesterolemia is 20 mg once daily.

The maximum rosuvastatin calcium tablet dose of 40 mg should be used only for those patients who have not achieved their LDL-C goal utilizing the 20 mg dose [Error! Hyperlink reference not valid.].

Rosuvastatin calcium tablets can be administered as a single dose at any time of day, with or without food. The tablet should be swallowed whole.

When initiating rosuvastatin calcium tablets therapy or switching from another HMG-CoA reductase inhibitor therapy, the appropriate rosuvastatin calcium tablets starting dose should first be utilized, and only then titrated according to the patient’s response and individualized goal of therapy.

After initiation or upon titration of rosuvastatin calcium tablets, lipid levels should be analyzed within 2 to 4 weeks and the dosage adjusted accordingly.

Pediatric use information for patients 7 to 17 years of age is approved for AstraZeneca’s CRESTOR (rosuvastatin calcium) tablets. However, due to AstraZeneca’s marketing exclusivity rights, this drug product is not labeled with that pediatric information.

2.3 Dosing in Asian Patients

In Asian patients, consider initiation of rosuvastatin calcium tablets therapy with 5 mg once daily due to increased rosuvastatin plasma concentrations. The increased systemic exposure should be taken into consideration when treating Asian patients not adequately controlled at doses up to 20 mg/day [Error! Hyperlink reference not valid. and Error! Hyperlink reference not valid.)].

2.4 Use with Concomitant Therapy

Patients taking cyclosporine

The dose of rosuvastatin calcium tablets should not exceed 5 mg once daily [Error! Hyperlink reference not valid., Error! Hyperlink reference not valid. and Error! Hyperlink reference not valid.].

Patients taking gemfibrozil

Avoid concomitant use of rosuvastatin calcium tablets with gemfibrozil. If concomitant use cannot be avoided, initiate rosuvastatin calcium tablets at 5 mg once daily. The dose of rosuvastatin calcium tablets should not exceed 10 mg once daily [Error! Hyperlink reference not valid., Error! Hyperlink reference not valid. and Error! Hyperlink reference not valid.].

Patients taking atazanavir and ritonavir, lopinavir and ritonavir, or simeprevir

Initiate rosuvastatin calcium tablets therapy with 5 mg once daily. The dose of rosuvastatin calcium tablets should not exceed 10 mg once daily [Error! Hyperlink reference not valid., Error! Hyperlink reference not valid. and Error! Hyperlink reference not valid.].

2.5 Dosing in Patients with Severe Renal Impairment

For patients with severe renal impairment (CLcr <30 mL/min/1.73 m2) not on hemodialysis, dosing of rosuvastatin calcium tablets should be started at 5 mg once daily and not exceed 10 mg once daily [Error! Hyperlink reference not valid. and Error! Hyperlink reference not valid.)].

3 DOSAGE FORMS & STRENGTHS

5 mg: Light yellow to yellow, round, bevel edged biconvex film coated tablets debossed with "H" on one side and "R3" on the other side.

10 mg: Light pink to pink, round, bevel edged biconvex film coated tablets debossed with "H" on one side and "R4" on the other side.

20 mg: Light pink to pink, round, bevel edged biconvex film coated tablets debossed with "H" on one side and "R5" on the other side.

40 mg: Light pink to pink, oval, bevel edged biconvex film coated tablets debossed with "H" on one side and "R6" on the other side.

4 CONTRAINDICATIONS

Rosuvastatin calcium tablets are contraindicated in the following conditions:

•Patients with a known hypersensitivity to any component of this product. Hypersensitivity reactions including rash, pruritus, urticaria, and angioedema have been reported with rosuvastatin calcium tablets [Error! Hyperlink reference not valid.)].

•Patients with active liver disease, which may include unexplained persistent elevations of hepatic transaminase levels [Error! Hyperlink reference not valid.)].

•Pregnancy [see Use in Specific Populations (8.1, Error! Hyperlink reference not valid.)].

•Lactation. Limited data indicate that rosuvastatin calcium is present in human milk. Because statins have the potential for serious adverse reactions in nursing infants, women who require rosuvastatin calcium tablets treatment should not breastfeed their infants Error! Hyperlink reference not valid.)].

5 WARNINGS AND PRECAUTIONS

5.1 Skeletal Muscle Effects

Cases of myopathy and rhabdomyolysis with acute renal failure secondary to myoglobinuria have been reported with HMG-CoA reductase inhibitors, including rosuvastatin calcium tablets. These risks can occur at any dose level, but are increased at the highest dose (40 mg).

Rosuvastatin calcium tablets should be prescribed with caution in patients with predisposing factors for myopathy (e.g., age ≥65 years, inadequately treated hypothyroidism, renal impairment).

The risk of myopathy during treatment with rosuvastatin calcium tablets may be increased with concurrent administration of some other lipid-lowering therapies (fibrates or niacin), gemfibrozil, cyclosporine, atazanavir/ritonavir, lopinavir/ritonavir, or simeprevir [see Dosage and Administration (2)and Drug Interactions (7)]. Cases of myopathy, including rhabdomyolysis, have been reported with HMG-CoA reductase inhibitors, including rosuvastatin, coadministered with colchicine, and caution should be exercised when prescribing rosuvastatin calcium tablets with colchicine [Error! Hyperlink reference not valid.)].

Rosuvastatin calcium tablets therapy should be discontinued if markedly elevated creatine kinase levels occur or myopathy is diagnosed or suspected. Rosuvastatin calcium tablets therapy should also be temporarily withheld in any patient with an acute, serious condition suggestive of myopathy or predisposing to the development of renal failure secondary to rhabdomyolysis (e.g., sepsis, hypotension, dehydration, major surgery, trauma, severe metabolic, endocrine, and electrolyte disorders, or uncontrolled seizures).

There have been rare reports of immune-mediated necrotizing myopathy (IMNM), an autoimmune myopathy, associated with statin use. IMNM is characterized by: proximal muscle weakness and elevated serum creatine kinase, which persist despite discontinuation of statin treatment; muscle biopsy showing necrotizing myopathy without significant inflammation; improvement with immunosuppressive agents.

All patients should be advised to promptly report to their physician unexplained muscle pain, tenderness, or weakness, particularly if accompanied by malaise or fever or if muscle signs and symptoms persist after discontinuing rosuvastatin calcium tablets.

5.2 Liver Enzyme Abnormalities

It is recommended that liver enzyme tests be performed before the initiation of rosuvastatin calcium tablets, and if signs or symptoms of liver injury occur.

Increases in serum transaminases [AST (SGOT) or ALT (SGPT)] have been reported with HMG-CoA reductase inhibitors, including rosuvastatin calcium tablets. In most cases, the elevations were transient and resolved or improved on continued therapy or after a brief interruption in therapy. There were two cases of jaundice, for which a relationship to rosuvastatin calcium tablets therapy could not be determined, which resolved after discontinuation of therapy. There were no cases of liver failure or irreversible liver disease in these trials.

In a pooled analysis of placebo-controlled trials, increases in serum transaminases to >3 times the upper limit of normal occurred in 1.1% of patients taking rosuvastatin calcium tablets versus 0.5% of patients treated with placebo.

There have been rare postmarketing reports of fatal and non-fatal hepatic failure in patients taking statins, including rosuvastatin. If serious liver injury with clinical symptoms and/or hyperbilirubinemia or jaundice occurs during treatment with rosuvastatin calcium tablets, promptly interrupt therapy. If an alternate etiology is not found, do not restart rosuvastatin calcium tablets.

Rosuvastatin calcium tablets should be used with caution in patients who consume substantial quantities of alcohol and/or have a history of chronic liver disease [Error! Hyperlink reference not valid.)]. Active liver disease, which may include unexplained persistent transaminase elevations, is a contraindication to the use of rosuvastatin calcium tablets [Error! Hyperlink reference not valid.].

5.3 Concomitant Coumarin Anticoagulants

Caution should be exercised when anticoagulants are given in conjunction with rosuvastatin calcium tablets because of its potentiation of the effect of coumarin-type anticoagulants in prolonging the prothrombin time/INR. In patients taking coumarin anticoagulants and rosuvastatin calcium tablets concomitantly, INR should be determined before starting rosuvastatin calcium tablets and frequently enough during early therapy to ensure that no significant alteration of INR occurs [Error! Hyperlink reference not valid.)].

5.4 Proteinuria and Hematuria

In the rosuvastatin calcium tablets clinical trial program, dipstick-positive proteinuria and microscopic hematuria were observed among rosuvastatin calcium tablets treated patients. These findings were more frequent in patients taking rosuvastatin calcium tablets 40 mg, when compared to lower doses of rosuvastatin calcium tablets or comparator HMG-CoA reductase inhibitors, though it was generally transient and was not associated with worsening renal function. Although the clinical significance of this finding is unknown, a dose reduction should be considered for patients on rosuvastatin calcium tablets therapy with unexplained persistent proteinuria and/or hematuria during routine urinalysis testing.

5.5 Endocrine Effects

Increases in HbA1c and fasting serum glucose levels have been reported with HMG-CoA reductase inhibitors, including rosuvastatin calcium tablets. Based on clinical trial data with rosuvastatin calcium tablets, in some instances these increases may exceed the threshold for the diagnosis of diabetes mellitus [Error! Hyperlink reference not valid.].

Although clinical studies have shown that rosuvastatin calcium tablets alone does not reduce basal plasma cortisol concentration or impair adrenal reserve, caution should be exercised if rosuvastatin calcium tablets are administered concomitantly with drugs that may decrease the levels or activity of endogenous steroid hormones such as ketoconazole, spironolactone, and cimetidine.

5.6 Risk of Allergic Reactions due to Tartrazine

This product contains FD&C Yellow No. 5 (tartrazine) which may cause allergic-type reactions (including bronchial asthma) in certain susceptible persons. Although the overall incidence of FD&C Yellow No. 5 (tartrazine) sensitivity in the general population is low, it is frequently seen in patients who also have aspirin hypersensitivity.

6 ADVERSE REACTIONS

The following serious adverse reactions are discussed in greater detail in other sections of the label:

•Rhabdomyolysis with myoglobinuria and acute renal failure and myopathy (including myositis) [Error! Hyperlink reference not valid.]

•Liver enzyme abnormalities [Error! Hyperlink reference not valid.)]

6.1 Clinical Studies Experience

Because clinical studies are conducted under widely varying conditions, adverse reaction rates observed in the clinical studies of a drug cannot be directly compared to rates in the clinical studies of another drug and may not reflect the rates observed in clinical practice.

In the rosuvastatin calcium tablets controlled clinical trials database (placebo or active-controlled) of 5394 patients with a mean treatment duration of 15 weeks, 1.4% of patients discontinued due to adverse reactions. The most common adverse reactions that led to treatment discontinuation were:

•myalgia

•abdominal pain

•nausea

The most commonly reported adverse reactions (incidence ≥2%) in the rosuvastatin calcium tablets controlled clinical trial database of 5394 patients were:

•headache

•myalgia

•abdominal pain

•asthenia

•nausea

Adverse reactions reported in ≥2% of patients in placebo-controlled clinical studies and at a rate greater than placebo are shown in Table 1. These studies had a treatment duration of up to 12 weeks.

Table 1. Adverse Reactions1 Reported in ≥2% of Patients Treated with Rosuvastatin Calcium Tablets and > Placebo in Placebo-Controlled Trials (% of Patients)

Adverse Reactions | Rosuvastatin Calcium Tablets 5 mg N=291 | Rosuvastatin Calcium Tablets 10 mg N=283 | Rosuvastatin Calcium Tablets 20 mg N=64 | Rosuvastatin Calcium Tablets 40 mg N=106 | Total Rosuvastatin Calcium Tablets 5 mg- 40 mg N=744 | Placebo N=382
Headache | 5.5 | 4.9 | 3.1 | 8.5 | 5.5 | 5
Nausea | 3.8 | 3.5 | 6.3 | 0 | 3.4 | 3.1
Myalgia | 3.1 | 2.1 | 6.3 | 1.9 | 2.8 | 1.3
Asthenia | 2.4 | 3.2 | 4.7 | 0.9 | 2.7 | 2.6
Constipation | 2.1 | 2.1 | 4.7 | 2.8 | 2.4 | 2.4

^1 Adverse reactions by COSTART preferred term.

Other adverse reactions reported in clinical studies were abdominal pain, dizziness, hypersensitivity (including rash, pruritus, urticaria, and angioedema) and pancreatitis. The following laboratory abnormalities have also been reported: dipstick-positive proteinuria and microscopic hematuria [Error! Hyperlink reference not valid.]; elevated creatine phosphokinase, transaminases, glucose, glutamyl transpeptidase, alkaline phosphatase, and bilirubin; and thyroid function abnormalities.

In a clinical trial, involving 981 participants treated with rosuvastatin 40 mg (n=700) or placebo (n=281) with a mean treatment duration of 1.7 years, 5.6% of subjects treated with rosuvastatin calcium tablets versus 2.8% of placebo-treated subjects discontinued due to adverse reactions. The most common adverse reactions that led to treatment discontinuation were: myalgia, hepatic enzyme increased, headache, and nausea.

Adverse reactions reported in ≥2% of patients and at a rate greater than placebo are shown in Table 2.

Table 2. Adverse Reactions1 Reported in ≥2% of Patients Treated with Rosuvastatin Calcium Tablets and > Placebo in a Trial (% of Patients)

Adverse Reactions | Rosuvastatin Calcium Tablets 40 mg N=700 | Placebo N=281
Myalgia | 12.7 | 12.1
Arthralgia | 10.1 | 7.1
Headache | 6.4 | 5.3
Dizziness | 4 | 2.8
Increased CPK | 2.6 | 0.7
Abdominal pain | 2.4 | 1.8
ALT >3x ULN^2 | 2.2 | 0.7

^1 Adverse reactions by MedDRA preferred term.

^2 Frequency recorded as abnormal laboratory value.

In a clinical trial, 17,802 participants were treated with rosuvastatin 20 mg (n=8901) or placebo (n=8901) for a mean duration of 2 years. A higher percentage of rosuvastatin-treated patients versus placebo-treated patients, 6.6% and 6.2%, respectively, discontinued study medication due to an adverse event, irrespective of treatment causality. Myalgia was the most common adverse reaction that led to treatment discontinuation. There was a significantly higher frequency of diabetes mellitus reported in patients taking rosuvastatin (2.8%) versus patients taking placebo (2.3%). Mean HbA1c was significantly increased by 0.1% in rosuvastatin-treated patients compared to placebo-treated patients. The number of patients with a HbA1c >6.5% at the end of the trial was significantly higher in rosuvastatin-treated versus placebo-treated patients [Error! Hyperlink reference not valid.].

Adverse reactions reported in ≥2% of patients and at a rate greater than placebo are shown in Table 3.

Table 3. Adverse Reactions1 Reported in ≥2% of Patients Treated with Rosuvastatin Calcium Tablets and > Placebo in a Trial (% of Patients)

Adverse Reactions | Rosuvastatin Calcium Tablets 20 mg N=8901 | Placebo N=8901
Myalgia | 7.6 | 6.6
Arthralgia | 3.8 | 3.2
Constipation | 3.3 | 3
Diabetes mellitus | 2.8 | 2.3
Nausea | 2.4 | 2.3

^1 Treatment-emergent adverse reactions by MedDRA preferred term.

6.2 Postmarketing Experience

The following adverse reactions have been identified during postapproval use of rosuvastatin calcium tablets: arthralgia, fatal and non-fatal hepatic failure, hepatitis, jaundice, thrombocytopenia, depression, sleep disorders (including insomnia and nightmares), peripheral neuropathy, interstitial lung disease and gynecomastia. Because these reactions are reported voluntarily from a population of uncertain size, it is not always possible to reliably estimate their frequency or establish a causal relationship to drug exposure.

There have been rare reports of immune-mediated necrotizing myopathy associated with statin use [Error! Hyperlink reference not valid.)].

There have been rare postmarketing reports of cognitive impairment (e.g., memory loss, forgetfulness, amnesia, memory impairment, confusion) associated with statin use. These cognitive issues have been reported for all statins. The reports are generally nonserious, and reversible upon statin discontinuation, with variable times to symptom onset (1 day to years) and symptom resolution (median of 3 weeks).

7 DRUG INTERACTIONS

7.1 Cyclosporine

Cyclosporine increased rosuvastatin exposure (AUC) 7‑fold. Therefore, in patients taking cyclosporine, the dose of rosuvastatin calcium tablets should not exceed 5 mg once daily [Error! Hyperlink reference not valid.), Error! Hyperlink reference not valid.), and Error! Hyperlink reference not valid.].

7.2 Gemfibrozil

Gemfibrozil significantly increased rosuvastatin exposure. Due to an observed increased risk of myopathy/rhabdomyolysis, combination therapy with rosuvastatin calcium tablets and gemfibrozil should be avoided. If used together, the dose of rosuvastatin calcium tablets should not exceed 10 mg once daily [Error! Hyperlink reference not valid.].

7.3 Protease Inhibitors

Coadministration of rosuvastatin with certain protease inhibitors has differing effects on rosuvastatin exposure. Simeprevir, which is a hepatitis C virus (HCV) protease inhibitor, or combinations of atazanavir/ritonavir or lopinavir/ritonavir, which are HIV-1 protease inhibitors, increase rosuvastatin exposure (AUC) up to threefold [see Table 4 – Error! Hyperlink reference not valid.)]. For these protease inhibitors, the dose of rosuvastatin calcium tablets should not exceed 10 mg once daily. The combinations of fosamprenavir/ritonavir or tipranavir/ritonavir, which are HIV-1 protease inhibitors, produce little or no change in rosuvastatin exposure. Caution should be exercised when rosuvastatin is coadministered with protease inhibitors [Error! Hyperlink reference not valid., Error! Hyperlink reference not valid. and Error! Hyperlink reference not valid.].

7.4 Coumarin Anticoagulants

Rosuvastatin calcium tablets significantly increased INR in patients receiving coumarin anticoagulants. Therefore, caution should be exercised when coumarin anticoagulants are given in conjunction with rosuvastatin calcium tablets. In patients taking coumarin anticoagulants and rosuvastatin calcium tablets concomitantly, INR should be determined before starting rosuvastatin calcium tablets and frequently enough during early therapy to ensure that no significant alteration of INR occurs [Error! Hyperlink reference not valid. and Error! Hyperlink reference not valid.].

7.5 Niacin

The risk of skeletal muscle effects may be enhanced when rosuvastatin calcium tablets are used in combination with lipid-modifying doses (≥1 g/day) of niacin; caution should be used when prescribing with rosuvastatin calcium tablets [see Warnings and Precautions Error! Hyperlink reference not valid.

7.6 Fenofibrate

When rosuvastatin calcium tablets were coadministered with fenofibrate, no clinically significant increase in the AUC of rosuvastatin or fenofibrate was observed. Because it is known that the risk of myopathy during treatment with HMG-CoA reductase inhibitors is increased with concomitant use of fenofibrates, caution should be used when prescribing fenofibrates with rosuvastatin calcium tablets [Error! Hyperlink reference not valid. and Error! Hyperlink reference not valid.)].

7.7 Colchicine

Cases of myopathy, including rhabdomyolysis, have been reported with HMG-CoA reductase inhibitors, including rosuvastatin, coadministered with colchicine, and caution should be exercised when prescribing rosuvastatin calcium tablets with colchicine [Error! Hyperlink reference not valid.)].

8 USE IN SPECIFIC POPULATIONS

8.1 Pregnancy

Risk Summary

Rosuvastatin calcium tablets are contraindicated for use in pregnant women since safety in pregnant women has not been established and there is no apparent benefit to therapy with rosuvastatin calcium tablets during pregnancy. Because HMG-CoA reductase inhibitors decrease cholesterol synthesis and possibly the synthesis of other biologically active substances derived from cholesterol, rosuvastatin calcium tablets may cause fetal harm when administered to pregnant women. Rosuvastatin calcium tablets should be discontinued as soon as pregnancy is recognized [Error! Hyperlink reference not valid.]. Limited published data on the use of rosuvastatin are insufficient to determine a drug-associated risk of major congenital malformations or miscarriage. In animal reproduction studies, there were no adverse developmental effects with oral administration of rosuvastatin during organogenesis at systemic exposures equivalent to a maximum recommended human dose (MRHD) of 40 mg/day in rats or rabbits (based on AUC and body surface area, respectively). In rats and rabbits, decreased pup/fetal survival occurred at 12 times and equivalent, respectively, to the MRHD of 40 mg/day [see Data].

The estimated background risk of major birth defects and miscarriage for the indicated population is unknown. In the U.S. general population, the estimated background risk of major birth defects and miscarriage in clinically recognized pregnancies is 2 to 4% and 15 to 20%, respectively.

Data

Human Data

Limited published data on rosuvastatin have not shown an increased risk of major congenital malformations or miscarriage. Rare reports of congenital anomalies have been received following intrauterine exposure to other statins. In a review of approximately 100 prospectively followed pregnancies in women exposed to simvastatin or lovastatin, the incidences of congenital anomalies, spontaneous abortions, and fetal deaths/stillbirths did not exceed what would be expected in the general population. The number of cases is adequate to exclude a ≥3 to 4-fold increase in congenital anomalies over the background incidence. In 89% of the prospectively followed pregnancies, drug treatment was initiated prior to pregnancy and was discontinued at some point in the first trimester when pregnancy was identified.

Animal Data

Rosuvastatin crosses the placenta in rats and rabbits and is found in fetal tissue and amniotic fluid at 3% and 20%, respectively, of the maternal plasma concentration following a single 25 mg/kg oral gavage dose on gestation day 16 in rats. A higher fetal tissue distribution (25% maternal plasma concentration) was observed in rabbits after a single oral gavage dose of 1 mg/kg on gestation day 18.

Rosuvastatin administration did not indicate a teratogenic effect in rats at ≤25 mg/kg/day or in rabbits ≤3 mg/kg/day (doses equivalent to the MRHD of 40 mg/day based on AUC and body surface area, respectively).

In female rats given 5, 15 and 50 mg/kg/day before mating and continuing through to gestation day 7 resulted in decreased fetal body weight (female pups) and delayed ossification at 50 mg/kg/day (10 times the human exposure at the MRHD dose of 40 mg/day based on AUC).

In pregnant rats given 2, 10 and 50 mg/kg/day of rosuvastatin from gestation day 7 through lactation day 21 (weaning), decreased pup survival occurred at 50 mg/kg/day (dose equivalent to 12 times the MRHD of 40 mg/day based body surface area).

In pregnant rabbits given 0.3, 1, and 3 mg/kg/day of rosuvastatin from gestation day 6 to day 18, decreased fetal viability and maternal mortality was observed at 3 mg/kg/day (dose equivalent to the MRHD of 40 mg/day based on body surface area).

8.2 Lactation

Risk Summary

Rosuvastatin use is contraindicated during breastfeeding [see Contraindications (4)]. Limited data indicate that rosuvastatin calcium is present in human milk. There is no available information on the effects of the drug on the breastfed infant or the effects of the drug on milk production. Because of the potential for serious adverse reactions in a breastfed infant, advise patients that breastfeeding is not recommended during treatment with rosuvastatin calcium.

8.3 Females and Males of Reproductive Potential

Contraception

Rosuvastatin calcium may cause fetal harm when administered to a pregnant womanError! Hyperlink reference not valid.. Advise females of reproductive potential to use effective contraception during treatment with rosuvastatin calcium.

8.4 Pediatric Use

Pediatric use information for patients 7 to 17 years of age is approved for AstraZeneca's CRESTOR (rosuvastatin calcium) tablets. However, due to AstraZeneca’s marketing exclusivity rights, this drug product is not labeled with that pediatric information.

8.5 Geriatric Use

Of the 10,275 patients in clinical studies with rosuvastatin calcium tablets, 3159 (31%) were 65 years and older, and 698 (6.8%) were 75 years and older. No overall differences in safety or effectiveness were observed between these subjects and younger subjects, and other reported clinical experience has not identified differences in responses between the elderly and younger patients, but greater sensitivity of some older individuals cannot be ruled out. Elderly patients are at higher risk of myopathy and rosuvastatin calcium tablets should be prescribed with caution in the elderly [see Warnings and Precautions (5.1) andError! Hyperlink reference not valid.].

8.6 Renal Impairment

Rosuvastatin exposure is not influenced by mild to moderate renal impairment (CLcr ≥30 mL/min/1.73 m2). Exposure to rosuvastatin is increased to a clinically significant extent in patients with severe renal impairment (CLcr <30 mL/min/1.73 m2) who are not receiving hemodialysis and dose adjustment is required [see Dosage and Administration Error! Hyperlink reference not valid. Warnings and Precautions Error! Hyperlink reference not valid. and Error! Hyperlink reference not valid.)].

8.7 Hepatic Impairment

Rosuvastatin calcium tablets are contraindicated in patients with active liver disease, which may include unexplained persistent elevations of hepatic transaminase levels. Chronic alcohol liver disease is known to increase rosuvastatin exposure; rosuvastatin calcium tablets should be used with caution in these patients [Error! Hyperlink reference not valid., Error! Hyperlink reference not valid. and Error! Hyperlink reference not valid.)].

8.8 Asian Patients

Pharmacokinetic studies have demonstrated an approximate 2-fold increase in median exposure to rosuvastatin in Asian subjects when compared with Caucasian controls. Rosuvastatin calcium tablets dosage should be adjusted in Asian patients [see Dosage and Administration Error! Hyperlink reference not valid. and Error! Hyperlink reference not valid.)].

10 OVERDOSAGE

There is no specific treatment in the event of overdose. In the event of overdose, the patient should be treated symptomatically and supportive measures instituted as required. Hemodialysis does not significantly enhance clearance of rosuvastatin.

11 DESCRIPTION

Rosuvastatin calcium is a synthetic lipid-lowering agent for oral administration.

The chemical name for rosuvastatin calcium is (3R, 5S, 6E) -7-[4-(4-Fluorophenyl)-6-(1-methylethyl)-2-[methyl (methylsulfonyl) amino]-5-pyrimidinyl]-3,5-dihydroxy-6-heptenoic acid calcium salt with the following structural formula:

The molecular formula for rosuvastatin calcium is (C22H27FN3O6S)2Ca and the molecular weight is 1001.14. Rosuvastatin calcium is a white to almost white powder that is sparingly soluble in methanol. Rosuvastatin calcium is a hydrophilic compound with a partition coefficient of 1.14 by HPLC.

Rosuvastatin calcium tablets for oral administration contain 5, 10, 20, or 40 mg of rosuvastatin and the following inactive ingredients: Each tablet contains: crospovidone, FD&C blue #2/indigo carmine aluminum lake, FD&C red #40/allura red AC aluminum lake, hydroxypropyl cellulose, hypromellose, lactose monohydrate, magnesium stearate, microcrystalline cellulose, sodium bicarbonate, talc, titanium dioxide and triacetin. Additionally 5 mg tablets contain FD&C yellow #5/tartrazine aluminum lake and 10 mg, 20 mg and 40 mg tablets contain FD&C yellow #6/sunset yellow FCF aluminum lake.

12 CLINICAL PHARMACOLOGY

12.1 Mechanism of Action

Rosuvastatin calcium tablets are a selective and competitive inhibitor of HMG-CoA reductase, the rate-limiting enzyme that converts 3-hydroxy-3-methylglutaryl coenzyme A to mevalonate, a precursor of cholesterol. In vivo studies in animals, and in vitro studies in cultured animal and human cells have shown rosuvastatin to have a high uptake into, and selectivity for, action in the liver, the target organ for cholesterol lowering. In in vivo and in vitro studies, rosuvastatin produces its lipid-modifying effects in two ways. First, it increases the number of hepatic LDL receptors on the cell-surface to enhance uptake and catabolism of LDL. Second, rosuvastatin inhibits hepatic synthesis of VLDL, which reduces the total number of VLDL and LDL particles.

12.3 Pharmacokinetics

Absorption

In clinical pharmacology studies in man, peak plasma concentrations of rosuvastatin were reached 3 to 5 hours following oral dosing. Both Cmax and AUC increased in approximate proportion to rosuvastatin calcium tablets dose. The absolute bioavailability of rosuvastatin is approximately 20%.

Administration of rosuvastatin calcium tablets with food did not affect the AUC of rosuvastatin.

The AUC of rosuvastatin does not differ following evening or morning drug administration.

Distribution

Mean volume of distribution at steady-state of rosuvastatin is approximately 134 liters. Rosuvastatin is 88% bound to plasma proteins, mostly albumin. This binding is reversible and independent of plasma concentrations.

Metabolism

Rosuvastatin is not extensively metabolized; approximately 10% of a radiolabeled dose is recovered as metabolite. The major metabolite is N-desmethyl rosuvastatin, which is formed principally by cytochrome P450 \ 2C9, and in vitro studies have demonstrated that N-desmethyl rosuvastatin has approximately one-sixth to one-half the HMG-CoA reductase inhibitory activity of the parent compound. Overall, greater than 90% of active plasma HMG-CoA reductase inhibitory activity is accounted for by the parent compound.

Excretion

Following oral administration, rosuvastatin and its metabolites are primarily excreted in the feces (90%). The elimination half-life (t1/2) of rosuvastatin is approximately 19 hours.

After an intravenous dose, approximately 28% of total body clearance was via the renal route, and 72% by the hepatic route.

Specific Populations

Race

A population pharmacokinetic analysis revealed no clinically relevant differences in pharmacokinetics among Caucasian, Hispanic, and Black or Afro-Caribbean groups. However, pharmacokinetic studies, including one conducted in the US, have demonstrated an approximate 2-fold elevation in median exposure (AUC and Cmax) in Asian subjects when compared with a Caucasian control group.

Gender

There were no differences in plasma concentrations of rosuvastatin between men and women.

Pediatric use information for patients ages 8 to less than 10 years is approved for AstraZeneca's CRESTOR (rosuvastatin calcium) tablets. However, due to AstraZeneca’s marketing exclusivity rights, this drug product is not labeled with that pediatric information.

Geriatric

There were no differences in plasma concentrations of rosuvastatin between the nonelderly and elderly populations (age ≥65 years).

Renal Impairment

Mild to moderate renal impairment (CLcr ≥30 mL/min/1.73 m2) had no influence on plasma concentrations of rosuvastatin. However, plasma concentrations of rosuvastatin increased to a clinically significant extent (about 3-fold) in patients with severe renal impairment (CLcr <30 mL/min/1.73 m2) not receiving hemodialysis compared with healthy subjects (CLcr >80 mL/min/1.73 m^2).

Hemodialysis

Steady-state plasma concentrations of rosuvastatin in patients on chronic hemodialysis were approximately 50% greater compared with healthy volunteer subjects with normal renal function.

Hepatic Impairment

In patients with chronic alcohol liver disease, plasma concentrations of rosuvastatin were modestly increased.

In patients with Child-Pugh A disease, Cmax and AUC were increased by 60% and 5%, respectively, as compared with patients with normal liver function. In patients with Child-Pugh B disease, Cmax and AUC were increased 100% and 21%, respectively, compared with patients with normal liver function.

Drug-Drug Interactions

Rosuvastatin clearance is not dependent on metabolism by cytochrome P450 3A4 to a clinically significant extent.

Rosuvastatin is a substrate for certain transporter proteins including the hepatic uptake transporter organic anion-transporting polyprotein 1B1 (OATP1B1) and efflux transporter breast cancer resistance protein (BCRP). Concomitant administration of rosuvastatin calcium tablets with medications that are inhibitors of these transporter proteins (e.g. cyclosporine, certain HIV protease inhibitors) may result in increased rosuvastatin plasma concentrations and an increased risk of myopathy [Error! Hyperlink reference not valid.]. It is recommended that prescribers consult the relevant product information when considering administration of such products together with rosuvastatin calcium tablets.

Table 4. Effect of Coadministered Drugs on Rosuvastatin Systemic Exposure

Coadm i n i st e r ed drug and dos i ng reg imen | R os uvas t a t in
 |  | Mean Ratio (ratio with/without) coadministered drug) No Effect=1
 | Dose (m g)^1 | Change in AUC | Change inCmax
C y closporine – stab le d o se required (75 mg – 200 mg B ID) | 10 mg QD for 10 d a ys | 7.1 ^2 | 11 ^2
At a z an avi r/ riton avir co mbin ation 300 m g /100 mg QD for 8 d a ys | 10 mg | 3.1^2 | 7^2
Simeprevir 150 mg QD, 7 days | 10 mg , single dose | 2.8^2 (2.3-3.4)^3 | 3.2^2 (2.6-3.9)^3
L opinavir/ritonav ir com b ination 400 m g/100 mg B ID for 17 d a ys | 20 mg QD for 7 d a ys | 2.1^2 (1.7-2.6)^3 | 5^2 (3.4-6.4)^3
Gemfibro z il 600 mg B ID for 7 d a ys | 80 mg | 1.9 ^2 (1.6-2.2) ^3 | 2.2‑^2 (1.8-2.7) ^3
Eltrombopag 75 mg QD, 5 d a ys | 10 mg | 1.6 (1.4-1.7)^3 | 2 (1.8-2.3) ^3
Darunavir 600 m g /riton a vir 100 mg B ID, 7 d a ys | 10 mg QD for 7 d a ys | 1.5 (1-2.1) ^3 | 2.4 (1.6-3.6) ^3
Tip ran avi r/ riton avir combin ation 500 m g/200 mg B ID for 11 d a ys | 10 mg | 1.4 (1.2-1.6) ^3 | 2.2 (1.8-2.7) ^3
Droned a rone 400 mg BID | 10 mg | 1.4
It r aco n a z ole 200 mg QD, 5 d a ys | 10 mg or 80 mg | 1.4 (1.2-1.6) ^3 1.3 (1.1-1.4) ^3 | 1.4 (1.2-1.5) ^3 1.2 (0.9-1.4)^3
Ez etimibe 10 mg QD, 14 da ys | 10 mg QD for 14 d a ys | 1.2 (0.9-1.6)^3 | 1.2 (0.8-1.6)^3
Fo sampre n avir/ritonavir 700 m g/100 mg B ID for 7 d a ys | 10 mg | 1.1 | 1.5
F enofib r ate 67 mg T ID f or 7 d a ys | 10 mg | ↔ | 1.2 (1.1-1.3)^3
Coadm i n i st e r ed drug and dos i ng reg imen | R os uvas t a t in
Rifampicin 450 mg QD, 7 d a ys | 20 mg | ↔
Aluminum & m a g n esium h yd ro xide combin ati on ant acid Administ ered simult an eous ly Administered 2 hours a p art | 40 mg 40 mg | 0.5^2 (0.4-0.5)^3 0.8 (0.7-0.9)^3 | 0.5^2 (0.4-0.6)^3 0.8 (0.7-1)^3
Ketocona z ole 200 mg B ID for 7 d a ys | 80 mg | 1 (0.8-1.2)^3 | 1 (0.7-1.3)^3
Fl ucona zo le 200 mg QD for 11 days | 80 mg | 1.1 (1-1.3)^3 | 1.1 (0.9-1.4)^3
E r yt hro m y cin 500 mg Q ID for 7 d a ys | 80 mg | 0.8 (0.7-0.9)^3 | 0.7 (0.5-0.9)^3

^1 Single dose unless otherwise noted.

^2 Clinically significant [see Dosage and Administration (2) and Warnings and Precautions (5)]

^3 Mean ratio with 90% CI (with/without coadministered drug, e.g., 1= no change, 0.7 = 30% decrease, 11=11 fold increase in exposure)

Table 5. Effect of Rosuvastatin Coadministration on Systemic Exposure to Other Drugs

Rosuvas t a t in Dos a ge Re g i men | Coadmi n i ste red Drug
 |  | Mean Ratio (ratio with/without coadministered drug) No Effect = 1
 | Name and D ose | Change in AUC | Change in C max
40 mg QD for 10 d a ys | W arfarin^1 25 mg si n gle dose | R - W arfarin 1 (1-1.1)^2 S - W arfarin 1.1 (1-1.1)^2 | R - W arfarin 1 (0.9-1)^2 S - W arfarin 1 (0.9-1.1)^2
40 mg QD for 12 d a ys | Di go xin 0.5 mg sin gle dose | 1 (0.9-1.2)^2 | 1 (0.9-1.2)^2
40 mg QD for 28 d a ys | Oral Contra c eptive (ethi n yl est radiol 0.035 mg & n o r g estrel 0.180, 0.215 and 0.250 mg) QD for 21 Days | EE 1.3 (1.2-1.3)^2 NG 1.3 (1.3-1.4)^2 | EE 1.3 (1.2-1.3)2 NG 1.2 (1.1-1.3)^2

EE = ethinyl estradiol, NG = norgestrel

^1 Clinically significant pharmacodynamic effects [Error! Hyperlink reference not valid.]

^2 Mean ratio with 90% CI (with/without coadministered drug, e.g., 1= no change, 0.7=30% decrease, 11=11-fold increase in exposure)

12.5 Pharmacogenomics

Disposition of HMG-CoA reductase inhibitors, including rosuvastatin, involves OATP1B1 and other transporter proteins. Higher plasma concentrations of rosuvastatin have been reported in very small groups of patients (n=3 to 5) who have two reduced function alleles of the gene that encodes OATP1B1 (SLCO1B1 521T > C). The frequency of this genotype (i.e., SLCO1B1 521 C/C) is generally lower than 5% in most racial/ethnic groups. The impact of this polymorphism on efficacy and/or safety of rosuvastatin has not been clearly established.

13 NONCLINICAL TOXICOLOGY

13.1 Carcinogenesis & Mutagenesis & Impairment Of Fertility

In a 104-week carcinogenicity study in rats at dose levels of 2, 20, 60, or 80 mg/kg/day by oral gavage, the incidence of uterine stromal polyps was significantly increased in females at 80 mg/kg/day at systemic exposure 20 times the human exposure at 40 mg/day based on AUC. Increased incidence of polyps was not seen at lower doses.

In a 107-week carcinogenicity study in mice given 10, 60, or 200 mg/kg/day by oral gavage, an increased incidence of hepatocellular adenoma/carcinoma was observed at 200 mg/kg/day at systemic exposures 20 times the human exposure at 40 mg/day based on AUC. An increased incidence of hepatocellular tumors was not seen at lower doses.

Rosuvastatin was not mutagenic or clastogenic with or without metabolic activation in the Ames test with Salmonella typhimurium and Escherichia coli, the mouse lymphoma assay, and the chromosomal aberration assay in Chinese hamster lung cells. Rosuvastatin was negative in the in vivo mouse micronucleus test.

In rat fertility studies with oral gavage doses of 5, 15, 50 mg/kg/day, males were treated for 9 weeks prior to and throughout mating and females were treated 2 weeks prior to mating and throughout mating until gestation day 7. No adverse effect on fertility was observed at 50 mg/kg/day (systemic exposures up to 10 times the human exposure at 40 mg/day based on AUC). In testicles of dogs treated with rosuvastatin at 30 mg/kg/day for one month, spermatidic giant cells were seen. Spermatidic giant cells were observed in monkeys after 6-month treatment at 30 mg/kg/day in addition to vacuolation of seminiferous tubular epithelium. Exposures in the dog were 20 times and in the monkey 10 times the human exposure at 40 mg/day based on body surface area. Similar findings have been seen with other drugs in this class.

13.2 Animal Pharmacology & OR Toxicology

Central Nervous System Toxicity

CNS vascular lesions, characterized by perivascular hemorrhages, edema, and mononuclear cell infiltration of perivascular spaces, have been observed in dogs treated with several other members of this drug class. A chemically similar drug in this class produced dose-dependent optic nerve degeneration (Wallerian degeneration of retinogeniculate fibers) in dogs, at a dose that produced plasma drug levels about 30 times higher than the mean drug level in humans taking the highest recommended dose. Edema, hemorrhage, and partial necrosis in the interstitium of the choroid plexus was observed in a female dog sacrificed moribund at day 24 at 90 mg/kg/day by oral gavage (systemic exposures 100 times the human exposure at 40 mg/day based on AUC). Corneal opacity was seen in dogs treated for 52 weeks at 6 mg/kg/day by oral gavage (systemic exposures 20 times the human exposure at 40 mg/day based on AUC). Cataracts were seen in dogs treated for 12 weeks by oral gavage at 30 mg/kg/day (systemic exposures 60 times the human exposure at 40 mg/day based on AUC). Retinal dysplasia and retinal loss were seen in dogs treated for 4 weeks by oral gavage at 90 mg/kg/day (systemic exposures 100 times the human exposure at 40 mg/day based on AUC). Doses ≤30 mg/kg/day (systemic exposures ≤60 times the human exposure at 40 mg/day based on AUC) did not reveal retinal findings during treatment for up to one year.

Juvenile Toxicology Study

In a juvenile study, rats were dosed by oral gavage with 10 or 50 mg/kg/day from weaning for 9 weeks prior to pairing, throughout pairing and up to the day before necropsy for males or up to gestation day 7 for females. No effects on sexual development, testicular and epididymal appearance or fertility were observed at either dose level.

Pediatric information is approved for AstraZeneca’s CRESTOR (rosuvastatin calcium) tablets. However, due to AstraZeneca's marketing exclusivity rights, this drug product is not labeled with that pediatric information.

14 CLINICAL STUDIES

14.3 Hypertriglyceridemia

Dose-Response Study: In a double-blind, placebo-controlled dose-response study in patients with baseline TG levels from 273 to 817 mg/dL, rosuvastatin calcium tablets given as a single daily dose (5 to 40 mg) over 6 weeks significantly reduced serum TG levels (Table 9).

Table 9. Dose-Response in Patients with Primary Hypertriglyceridemia over 6 Weeks Dosing Median (Min, Max) Percent Change from Baseline

Dose | Placebo (n=26) | Rosuvastatin Calcium Tablets 5 mg (n=25) | Rosuvastatin Calcium Tablets 10 mg (n=23) | Rosuvastatin Calcium Tablets 20 mg (n=27) | Rosuvastatin Calcium Tablets 40 mg (n=25)
T ri gl ycer ides | 1 (-40, 72) | -21 (-58, 38) | -37 (-65, 5) | -37 (-72, 11) | -43 (-80, - 7)
nonHD L -C | 2 (- 13, 19) | -29 (-43, - 8) | -49 (-59, -20) | -43 (-74, 12) | -51 (-62, - 6)
V LDL -C | 2 (-36, 53) | -25 (-62, 49) | -48 (-72, 14) | -49 (-83, 20) | -56 (-83, 10)
T ot al -C | 1 (-13, 17) | -24 (-40, - 4) | -40 (-51, -14) | -34 (-61 , -11) | -40 (-51, - 4)
LD L -C | 5 (- 30, 52) | -28 (-71, 2) | -45 (-59, 7) | -31 (-66, 34) | -43 (-61, - 3)
HD L -C | -3 (- 25, 18) | 3 (-38, 33) | 8 (-8, 24) | 22 (-5, 50) | 17 (-14, 63)

14.4 Primary Dysbetalipoproteinemia (Type III Hyperlipoproteinemia)

In a randomized, multicenter, double-blind crossover study, 32 patients (27 with є2/є2 and 4 with apo E mutation [Arg145Cys] with primary dysbetalipoproteinemia (Type III Hyperlipoproteinemia) entered a 6-week dietary lead-in period on the NCEP Therapeutic Lifestyle Change (TLC) diet. Following dietary lead-in, patients were randomized to a sequence of treatments in conjunction with the TLC diet for 6 weeks each: rosuvastatin 10 mg followed by rosuvastatin 20 mg or rosuvastatin 20 mg followed by rosuvastatin 10 mg. Rosuvastatin calcium tablets reduced non HDL-C (primary end point) and circulating remnant lipoprotein levels. Results are shown in the table below.

Table 10. Lipid-modifying Effects of Rosuvastatin 10 mg and 20 mg in Primary Dysbetalipoproteinemia (Type III hyperlipoproteinemia) After Six Weeks by Median Percent Change (95% CI) from Baseline (N=32)

 | Median at Baseline (mg/dL) | Median percent change from baseline (95 % CI) Rosuvastatin Calcium Tablets 10 mg | Median percent change from baseline (95% CI) Rosuvastatin Calcium Tablets 20 mg
Total-C | 342.5 | -43.3 (-46.9,-37.5) | -47.6 (-51.6,-42.8)
Triglycerides | 503.5 | -40.1 (-44.9, -33.6) | -43 (-52.5, -33.1)
NonHDL-C | 294.5 | -48.2 (-56.7, -45.6) | -56.4 (-61.4, -48.5)
VLDL-C + IDL- C | 209.5 | -46.8 (-53.7, -39.4) | -56.2 (-67.7, -43.7)
LDL-C | 112.5 | -54.4 (-59.1, -47.3) | -57.3 (-59.4, -52.1)
HDL-C | 35.5 | 10.2 (1.9, 12.3) | 11.2 (8.3, 20.5)
RLP-C | 82 | -56.4 (-67.1, -49) | -64.9 (-74, -56.6)
Apo-E | 16 | -42.9 (-46.3, -33.3) | -42.5 (-47.1, -35.6)

14.5 Homozygous Familial Hypercholesterolemia

Dose-Titration Study: In an open-label, forced-titration study, homozygous FH patients (n=40, 8 to 63 years) were evaluated for their response to rosuvastatin calcium tablets 20 to 40 mg titrated at a 6-week interval. In the overall population, the mean LDL-C reduction from baseline was 22%. About one-third of the patients benefited from increasing their dose from 20 mg to 40 mg with further LDL lowering of greater than 6%. In the 27 patients with at least a 15% reduction in LDL-C, the mean LDL-C reduction was 30% (median 28% reduction). Among 13 patients with an LDL-C reduction of <15%, 3 had no change or an increase in LDL-C. Reductions in LDL-C of 15% or greater were observed in 3 of 5 patients with known receptor negative status.

Pediatric use information for patients 7 to 17 years of age is approved for AstraZeneca’s CRESTOR (rosuvastatin calcium) tablets. However, due to AstraZeneca’s marketing exclusivity rights, this drug product is not labeled with that pediatric information.

16 HOW SUPPLIED/STORAGE AND HANDLING

Rosuvastatin Calcium Tablets are supplied as:

20 mg: Light pink to pink, round, bevel edged biconvex film coated tablets debossed with 'H' on one side and 'R5' on the other side. They are supplied as follows.

Bottle of 30 Tablets NDC 71205-044-30

Bottle of 90 Tablets NDC 71205-044-90

Storage

Store at 20º to 25ºC (68º to 77ºF) [see USP Controlled Room Temperature]. Protect from moisture.

17 PATIENT COUNSELING INFORMATION

Advise the patient to read the FDA-approved patient labeling (Patient Information).

Patients should be instructed not to take 2 doses of rosuvastatin calcium tablets within 12 hours of each other.

Skeletal Muscle Effects

Patients should be advised to report promptly unexplained muscle pain, tenderness, or weakness, particularly if accompanied by malaise or fever or if these muscle signs or symptoms persist after discontinuing rosuvastatin calcium tablets.

Concomitant Use of Antacids

When taking rosuvastatin calcium tablets with an aluminum and magnesium hydroxide combination antacid, the antacid should be taken at least 2 hours after rosuvastatin calcium tablets administration.

Embryofetal Toxicity

Advise females of reproductive potential of the risk to a fetus, to use effective contraception during treatment, and to inform their healthcare provider of a known or suspected pregnancy. [Error! Hyperlink reference not valid. and Error! Hyperlink reference not valid., Error! Hyperlink reference not valid.)].

Lactation

Advise women not to breastfeed during treatment with rosuvastatin calcium tablets [Error! Hyperlink reference not valid. and Error! Hyperlink reference not valid.)].

Liver Enzymes

It is recommended that liver enzyme tests be performed before the initiation of rosuvastatin calcium tablets and if signs or symptoms of liver injury occur. All patients treated with rosuvastatin calcium tablets should be advised to promptly report any symptoms that may indicate liver injury, including fatigue, anorexia, right upper abdominal discomfort, dark urine or jaundice.

Manufactured for:

Camber Pharmaceuticals, Inc.

Piscataway, NJ 08854

Manufactured by:

HETEROTM

HETERO LABS LIMITED 2038142

Unit V, Polepally, Jadcherla,
Mahaboob Nagar-509 301, India.

Barcode

Revised: July 2016

Repackaged and Relabeled by:

Proficient Rx LP

Thousand Oaks, CA 91320

PATIENT INFORMATION

Rosuvastatin Calcium

(roe-soo-va-STAT-in KAL-see-um)

Tablets

Read this Patient Information carefully before you start taking rosuvastatin calcium tablets and each time you get a refill. If you have any questions about rosuvastatin calcium tablets, ask your doctor. Only your doctor can determine if rosuvastatin calcium tablets are right for you.

What is rosuvastatin calcium tablet?

Rosuvastatin calcium tablet is a prescription medicine that contains a cholesterol-lowering medicine called rosuvastatin calcium. Most of the cholesterol in your blood is made in the liver. Rosuvastatin calcium tablets works by reducing cholesterol in two ways: rosuvastatin calcium tablets blocks an enzyme in the liver causing the liver to make less cholesterol, and rosuvastatin calcium tablets increases the uptake and breakdown by the liver of cholesterol already in the blood.

• Rosuvastatin calcium tablets are used along with diet to:

o lower the level of your “bad” cholesterol (LDL)

o increase the level of your “good” cholesterol (HDL)

o lower the level of fat in your blood (triglycerides)

• Rosuvastatin calcium tablets are used to treat:

o adults who cannot control their cholesterol levels by diet and exercise alone

It is not known if rosuvastatin calcium tablets are safe and effective in people who have Fredrickson Type I and V dyslipidemias.

Pediatric use information for patients 7 to 17 years of age is approved for AstraZeneca’s CRESTOR (rosuvastatin calcium) tablets. However, due to AstraZeneca’s marketing exclusivity rights, this drug product is not labeled with that pediatric information.

Who should not take rosuvastatin calcium tablets?

Do not take rosuvastatin calcium tablets if you:

• are allergic to rosuvastatin calcium or any of the ingredients in rosuvastatin calcium tablets. See the end of this leaflet for a complete list of ingredients in rosuvastatin calcium tablets.

• have liver problems.

• are pregnant or think you may be pregnant, or are planning to become pregnant. Rosuvastatin calcium tablets may harm your unborn baby. If you become pregnant, stop taking rosuvastatin calcium tablets and call your doctor right away. If you are not planning to become pregnant you should use effective birth control (contraception) while you are taking rosuvastatin calcium tablets.

• are breastfeeding. Medicines like rosuvastatin calcium can pass into your breast milk and may harm your baby.

What should I tell my doctor before and while taking rosuvastatin calcium tablets?

Tell your doctor if you:

• have unexplained muscle aches or weakness

• have or have had kidney problems

• have or have had liver problems

• drink more than 2 glasses of alcohol daily

• have thyroid problems

• are 65 years of age or older

• are of Asian descent

• are pregnant or think you may be pregnant, or are planning to become pregnant

• are breastfeeding

Tell your doctor about all the medicines you take, including prescription and over-the-counter medicines, vitamins, and herbal supplements.

Talk to your doctor before you start taking any new medicines.

Taking rosuvastatin calcium tablets with certain other medicines may affect each other causing side effects. Rosuvastatin calcium tablets may affect the way other medicines work, and other medicines may affect how rosuvastatin calcium tablets works.

Especially tell your doctor if you take:

• cyclosporine (a medicine for your immune system)

• gemfibrozil (a fibric acid medicine for lowering cholesterol)

• anti-viral medicines including HIV or hepatitis C protease inhibitors (such as lopinavir, ritonavir, fosamprenavir, tipranavir, atazanavir, or simeprevir)

• certain anti-fungal medicines (such as itraconazole, ketoconazole and fluconazole)

• coumarin anticoagulants (medicines that prevent blood clots, such as warfarin)

• niacin or nicotinic acid

• fibric acid derivatives (such as fenofibrate)

• colchicine (a medicine used to treat gout)

Ask your doctor or pharmacist for a list of these medicines if you are not sure.

Know all of the medicines you take. Keep a list of them to show your doctor and pharmacist when you get new medicine.

How should I take rosuvastatin calcium tablets?

• Take rosuvastatin calcium tablets exactly as your doctor tells you to take it.

• Take rosuvastatin calcium tablets, by mouth, 1 time each day. Swallow the tablet whole.

• Rosuvastatin calcium tablets can be taken at any time of day, with or without food.

• Do not change your dose or stop rosuvastatin calcium tablets without talking to your doctor, even if you are feeling well.

• Your doctor may do blood tests to check your cholesterol levels before and during your treatment with rosuvastatin calcium tablets. Your doctor may change your dose of rosuvastatin calcium tablets if needed.

• Your doctor may start you on a cholesterol lowering diet before giving you rosuvastatin calcium tablets. Stay on this diet when you take rosuvastatin calcium tablets.

• Wait at least 2 hours after taking rosuvastatin calcium tablets to take an antacid that contains a combination of aluminum and magnesium hydroxide.

• If you miss a dose of rosuvastatin calcium tablets, take it as soon as you remember. However, do not take 2 doses of rosuvastatin calcium tablets within 12 hours of each other.

• If you take too much rosuvastatin calcium tablets or overdose, call your doctor or go to the nearest hospital emergency room right away.

What are the Possible Side Effects of rosuvastatin calcium tablets?

Rosuvastatin calcium tablets may cause serious side effects, including:

• Muscle pain, tenderness and weakness (myopathy). Muscle problems, including muscle breakdown, can be serious in some people and rarely cause kidney damage that can lead to death. Tell your doctor right away if:

o you have unexplained muscle pain, tenderness, or weakness, especially if you have a fever or feel more tired than usual, while you take rosuvastatin calcium tablets.

o you have muscle problems that do not go away even after your doctor has told you to stop taking rosuvastatin calcium tablets. Your doctor may do further tests to diagnose the cause of your muscle problems.

Your chances of getting muscle problems are higher if you:

o are taking certain other medicines while you take rosuvastatin calcium tablets

o are 65 years of age or older

o have thyroid problems (hypothyroidism) that are not controlled

o have kidney problems

o are taking higher doses of rosuvastatin calcium tablets.

• Liver problems. Your doctor should do blood tests to check your liver before you start taking rosuvastatin calcium tablets and if you have symptoms of liver problems while you take rosuvastatin calcium tablets. Call your doctor right away if you have any of the following symptoms of liver problems:

o feel unusually tired or weak
o loss of appetite

o upper belly pain

o dark urine

o yellowing of your skin or the whites of your eyes

The most common side effects may include: headache, muscle aches and pains, abdominal pain, weakness, and nausea.

Additional side effects that have been reported with rosuvastatin calcium tablets include memory loss and confusion.

Tell your doctor if you have any side effect that bothers you or that does not go away.

These are not all the possible side effects of rosuvastatin calcium tablets. For more information, ask your doctor or pharmacist.

Call your doctor for medical advice about side effects. You may report side effects to FDA at 1-800-FDA-1088.

How should I store rosuvastatin calcium tablets?

• Store rosuvastatin calcium tablet at room temperature, between 68° to 77°F (20° to 25°C) and in a dry place.

• Safely throw away medicine that is out of date or no longer needed.

Keep rosuvastatin calcium tablets and all medicines out of the reach of children.

What are the Ingredients in rosuvastatin calcium tablets?

Active Ingredient: rosuvastatin as rosuvastatin calcium

Inactive Ingredients: crospovidone, FD&C blue #2/indigo carmine aluminum lake, FD&C red #40/allura red AC aluminum lake, hydroxypropyl cellulose, hypromellose, lactose monohydrate, magnesium stearate, microcrystalline cellulose, sodium bicarbonate, talc, titanium dioxide and triacetin. Additionally 5 mg tablets contain FD&C yellow #5/tartrazine aluminum lake and 10 mg, 20 mg and 40 mg tablets contain FD&C yellow #6/sunset yellow FCF aluminum lake.

General Information about the safe and effective use of rosuvastatin calcium tablets

Medicines are sometimes prescribed for purposes other than those listed in a Patient Information leaflet. Do not use rosuvastatin calcium tablets for a condition for which it was not prescribed. Do not give rosuvastatin calcium tablets to other people, even if they have the same medical condition you have. It may harm them.

You can ask your pharmacist or doctor for information about rosuvastatin calcium tablets that is written for health professionals.

Manufactured for:

Camber Pharmaceuticals, Inc.

Piscataway, NJ 08854

Manufactured by:

HETEROTM

HETERO LABS LIMITED

Unit V, Polepally, Jadcherla,

Mahaboob Nagar-509 301, India.

This Patient Information has been approved by the U.S. Food and Drug Administration.

Revised: July 2016

Repackaged and Relabeled by:

Proficient Rx LP

Thousand Oaks, CA 91320

PACKAGE LABEL.PRINCIPAL DISPLAY PANEL

20 mg 90s count